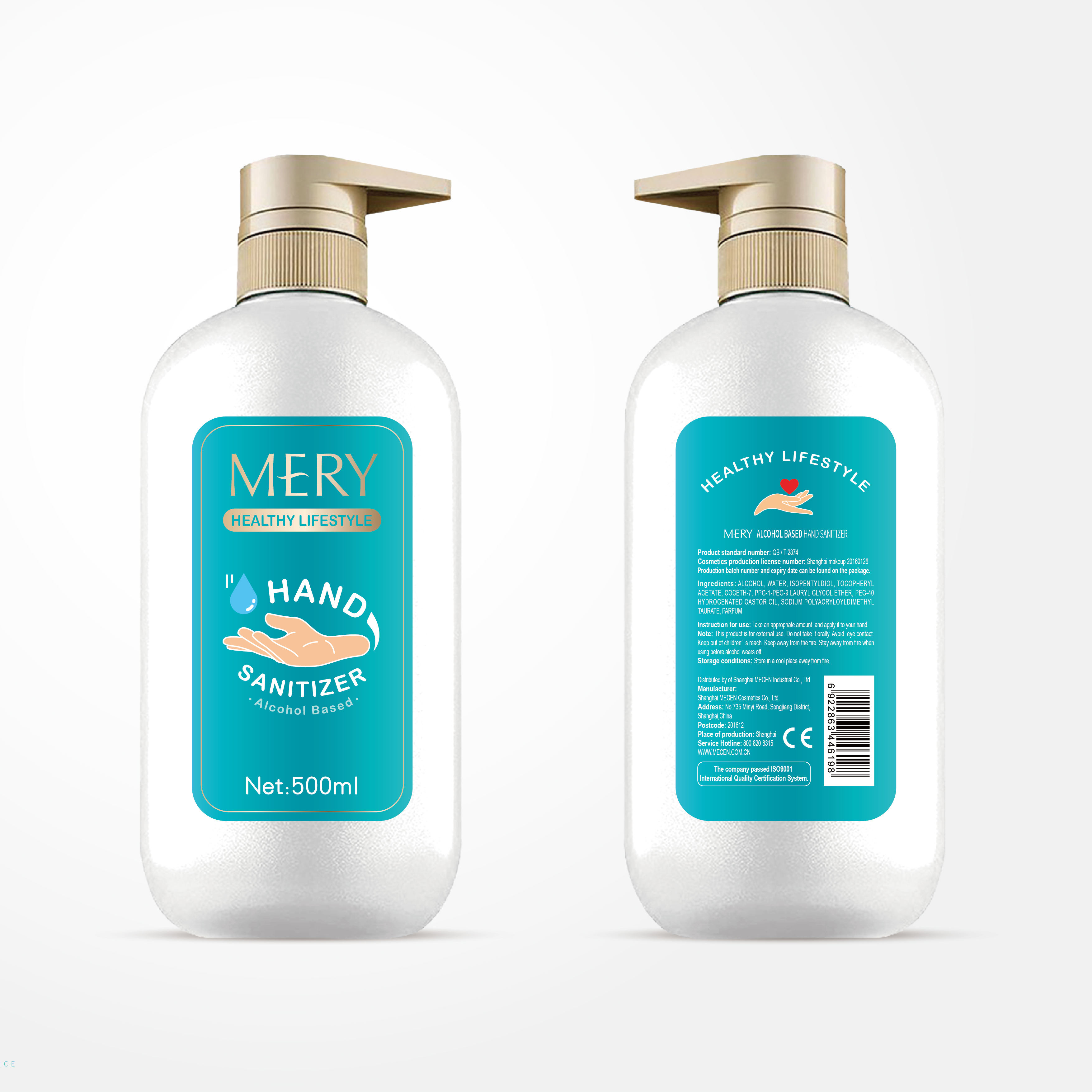 DRUG LABEL: mery alcohol based hand sanitizer
NDC: 54765-066 | Form: LIQUID
Manufacturer: Shanghai Mecen Cosmetics Co., Ltd.
Category: otc | Type: HUMAN OTC DRUG LABEL
Date: 20200421

ACTIVE INGREDIENTS: ALCOHOL 310 mL/500 mL
INACTIVE INGREDIENTS: WATER; .ALPHA.-TOCOPHEROL ACETATE; PPG-1-PEG-9 LAURYL GLYCOL ETHER; CARBOMER HOMOPOLYMER, UNSPECIFIED TYPE; SODIUM TAURATE; ISOPENTYLDIOL; COCETH-7; POLYOXYL 40 HYDROGENATED CASTOR OIL

WARNINGS

This product is for extemal use. Do not take it orally Avoid eye contact.

Keep out of children' s reach. Keep away from the fire.

Stay away from fire when using before alcohol wears off.

INACTIVE INGREDIENT

WATER、ISOPENTYLDIOL、TOCOPHERYL ACETATE、-7 COCETH-7、PPG-1-PEG-9 PPG-1-PEG-9 LAURYL GLYCOL ETHER、PEG-40 PEG-40 HYDROGENATED CASTOR OIL、SODIUM POLYACRYLOYLDIMETHYL TAURATE、PARFUM

DOSAGE AND ADMINISTRATION

Store in a cool place away from fire.

ACTIVE INGREDIENT

ethanol

keep out of reach of children

INDICATIONS AND USAGE

Take an appropriate amount and apply it to your hand.

PURPOSE

Disinfection
Sterilization
No Rinseing